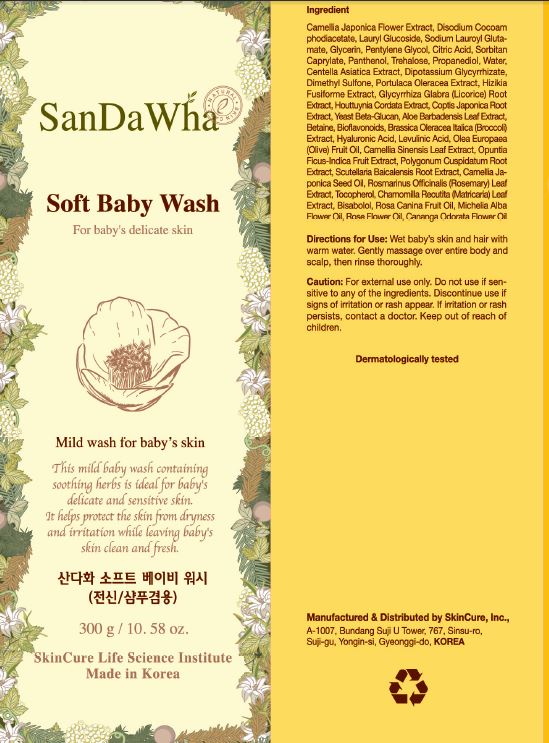 DRUG LABEL: SanDaWha Soft Baby Wash
NDC: 72289-0004 | Form: CREAM
Manufacturer: SKINCURE INC
Category: otc | Type: HUMAN OTC DRUG LABEL
Date: 20190223

ACTIVE INGREDIENTS: GLYCERIN 1.9345 g/100 g
INACTIVE INGREDIENTS: PANTHENOL; CITRIC ACID ACETATE; WATER

Drug Facts

ACTIVE INGREDIENT

glycerin

INACTIVE INGREDIENT

Camellia Japonica Flower Extract
Disodium Cocoamphodiacetate
Lauryl Glucoside
Sodium Lauroyl Glutamate
Glycerin
Pentylene Glycol
Citric Acid
Sorbitan Caprylate
Panthenol
Propanediol
Trehalose
Water(Aqua)
Centella Asiatica Extract
Dipotassium Glycyrrhizate
Dimethyl Sulfone
Portulaca Oleracea Extract
Hizikia Fusiforme Extract
Glycyrrhiza Glabra (Licorice) Root Extract
Houttuynia Cordata Extract
Coptis Japonica Root Extract
Yeast Beta-Glucan
Betaine
Hyaluronic Acid
Aloe Barbadensis Leaf Extract
Levulinic Acid
Olea Europaea (Olive) Fruit Oil
Camellia Sinensis Leaf Extract
Opuntia Ficus-Indica Fruit Extract
Polygonum Cuspidatum Root Extract
Scutellaria Baicalensis Root Extract
Camellia Japonica Seed Oil
Rosmarinus Officinalis (Rosemary) Leaf Extract
Tocopherol
Bioflavonoids
Chamomilla Recutita (Matricaria) Leaf Extract
Bisabolol
Rosa Canina Fruit Oil
Brassica Oleracea Italica (Broccoli) Extract
Michelia Alba Flower Oil
Rose Flower Oil
Cananga Odorata Flower Oil

PURPOSE

protect the skin from dryness and irritation while leaving baby's skin clean and fresh

keep out of reach of the children

INDICATIONS AND USAGE

Wet baby's skin and hair with warm water. Gently massage over entire body and scalp, then rinse thoroughly.

WARNINGS

for external use only

do not use if sensitive to any of the ingredients

discontinue use if signs of irritation or rash appear

if irritation or rash persists, contact a doctor

DOSAGE AND ADMINISTRATION

for external use only